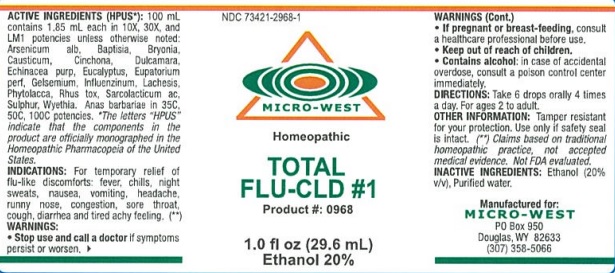 DRUG LABEL: TOTAL FLU CLD 1
NDC: 73421-2968 | Form: LIQUID
Manufacturer: White Manufacturing Inc. DBA Micro-West
Category: homeopathic | Type: HUMAN OTC DRUG LABEL
Date: 20211208

ACTIVE INGREDIENTS: ARSENIC TRIOXIDE 10 [hp_X]/29.6 mL; BAPTISIA TINCTORIA ROOT 10 [hp_X]/29.6 mL; BRYONIA ALBA ROOT 10 [hp_X]/29.6 mL; CAUSTICUM 10 [hp_X]/29.6 mL; CINCHONA BARK 10 [hp_X]/29.6 mL; SOLANUM DULCAMARA TOP 10 [hp_X]/29.6 mL; ECHINACEA PURPUREA 10 [hp_X]/29.6 mL; EUCALYPTUS GLOBULUS LEAF 10 [hp_X]/29.6 mL; EUPATORIUM PERFOLIATUM FLOWERING TOP 10 [hp_X]/29.6 mL; GELSEMIUM SEMPERVIRENS ROOT 10 [hp_X]/29.6 mL; INFLUENZA A VIRUS 10 [hp_X]/29.6 mL; LACHESIS MUTA VENOM 10 [hp_X]/29.6 mL; PHYTOLACCA AMERICANA ROOT 10 [hp_X]/29.6 mL; TOXICODENDRON PUBESCENS LEAF 10 [hp_X]/29.6 mL; LACTIC ACID, L- 10 [hp_X]/29.6 mL; SULFUR 10 [hp_X]/29.6 mL; WYETHIA HELENIOIDES ROOT 10 [hp_X]/29.6 mL; CAIRINA MOSCHATA HEART/LIVER AUTOLYSATE 35 [hp_C]/29.6 mL
INACTIVE INGREDIENTS: ALCOHOL; WATER

TOTAL FLU CLD 1

ACTIVE INGREDIENT

ACTIVE INGREDIENTS (HPUS*): 100 mL contains 1.85 mL each in 10X, 30X, and LM1 potencies unless otherwise noted: Arsenicum alb, Baptisia, Bryonia, Causticum, Cinchona, Dulcamara, Echinacea purp, Eucalyptus, Eupatorium perf, Gelsemium, Influenzinum, Lachesis, Phytolacca, Rhus tox, Sarcolacticum ac, Sulphur, Wyethia. Anas barbariae in 35C, 50C, 100C potencies.

*The letters "HPUS" indicate that the components in the products are officially monographed in the Homeopathic Pharmacopeia of the United States.

(**) Claims based on traditional homeopathic practice, not accepted medical evidence. Not FDA evaluated.

INDICATIONS AND USAGE

INDICATIONS: For temporary relief of flu-like discomforts: fever, chills, night sweats, nausea, vomiting, headache, runny nose, congestion, sore throat, cough, diarrhea and tired achy feeling. (**)

WARNINGS:

- Stop use and call a doctor if symptoms persist or worsen.
- If pregnant or breast-feeding, consult a healthcare professional before use.
- Keep out of reach of children.
- Contains alcohol: In case of accidental overdose, consult a poison control center immediately.

- Keep out of reach of children.

DOSAGE AND ADMINISTRATION

DIRECTIONS: Take 6 drops orally 4 times a day. For ages 2 to adult.

OTHER INFORMATION: Tamper resistant for your protection. Use only if safety seal is intact.

INACTIVE INGREDIENTS: Ethanol (20% v/v), Purified water.

QUESTIONS

Manufactured for:

MICRO-WEST

PO Box 950

Douglas, WY 82633

(307) 358-5066

PACKAGE LABEL

NDC 73421-2968-1

MICRO-WEST

Homeopathic

TOTAL FLU-CLD #1

Product #: 0968

1.0 fl oz (29.6 mL)

Ethanol 20%

PURPOSE

For temporary relief of flu-like discomforts: fever, chills, night sweats, nausea, vomiting, headache, runny nose, congestion, sore throat, cough, diarrhea and tired achy feeling. (**)